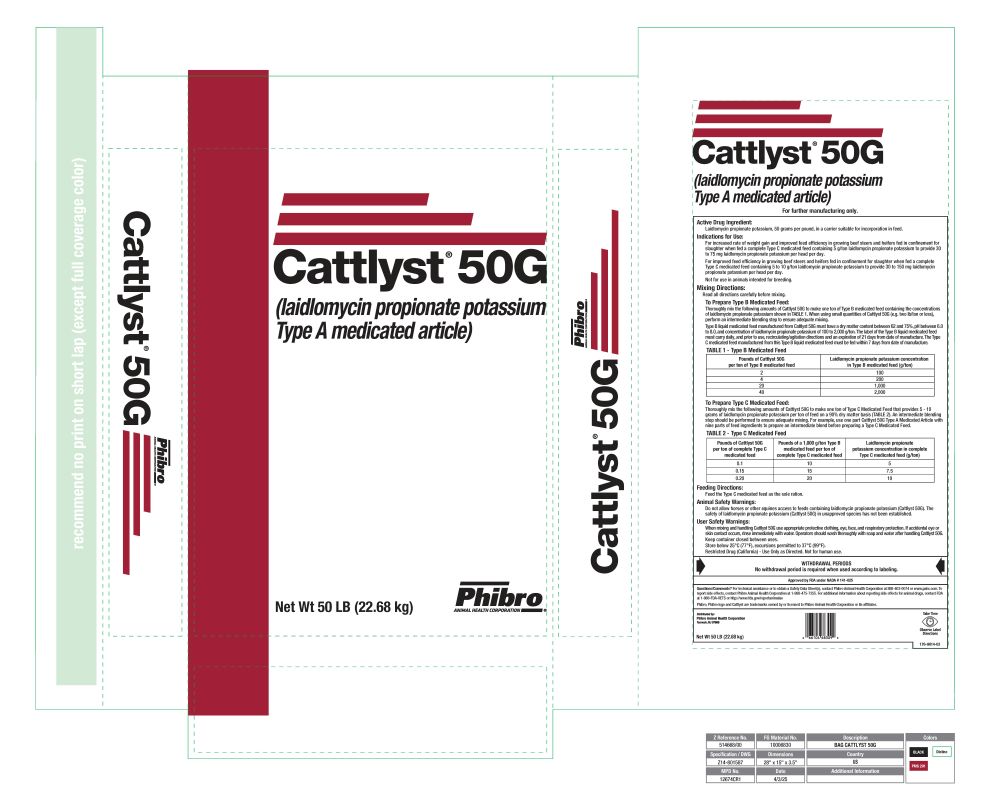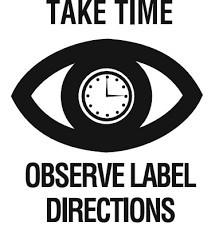 DRUG LABEL: Cattlyst
NDC: 66104-2000 | Form: GRANULE
Manufacturer: Phibro Animal Health
Category: animal | Type: OTC TYPE A MEDICATED ARTICLE ANIMAL DRUG LABEL
Date: 20260112

ACTIVE INGREDIENTS: LAIDLOMYCIN PROPIONATE POTASSIUM 50 g/0.45 kg

Cattlyst®
50G

Cattlyst 50G

Laidlomycin propionate potassium

Type A Medicated Article

Net Wt 50 LB (22.68 kg)

For further manufacturing only.

Active Drug Ingredient

Laidlomycin propionate potassium, 50 grams per pound, in a carrier suitable for incorporation in feed.

Weight Gain and Feed Efficiency

For increased rate of weight gain and improved feed efficiency in growing beef steers and heifers fed in confinement for slaughter when fed a complete Type C medicated feed containing 5 g/ton laidlomycin propionate potassium to provide 30 to 75 mg laidlomycin propionate potassium per head per day.

For improved feed efficiency in growing beef steers and heifers fed in confinement for slaughter when fed a complete Type C medicated feed containing 5 to 10 g/ton laidlomycin propionate potassium to provide 30 to 150 mg laidlomycin propionate potassium per head per day.

Not for use in animals intended for breeding.

Mixing And Feeding Instructions

Read all directions carefully before mixing and feeding.

Type B Medicated Feed

Thoroughly mix the following amounts of Cattlyst 50G to make one ton of Type B medicated feed containing the concentrations laidlomycin propionate potassium shown in TABLE 1. When using small quantities of Cattlyst 50G (e.g. two lb/ton or less), perform an intermediate blending step to ensure adequate mixing.

Type B liquid medicated feed manufactured from Cattlyst 50G must have a dry matter content between 62 and 75%, pH between 6.0 to 8.0, and concentration of laidlomycin propionate potassium of 100 to 2,000 g/ton. The label of the Type B liquid medicated feed must carry daily, and prior to use, recirculating/agitation directions and an expiration of 21 days from date of manufacture. The Type C medicated feed manufactured from this Type B liquid medicated feed must be fed within 7 days from date of manufacture.

TABLE 1 - Type B Medicated Feed
Pounds of Cattlyst 50G per ton of Type B medicated feed | Laidlomycin propionate potassium concentration in Type B medicated feed (g/ton)
2 | 100
4 | 200
20 | 1,000
40 | 2,000

Type C Medicated Feed

Thoroughly mix the following amounts of Cattlyst 50G to make one ton of Type C Medicated Feed that provides 5-10 grams of laidlomycin propionate potassium per ton of feed on a 90% dry matter basis (TABLE 2). An intermediate blending step should be performed to ensure adequate mixing. For example, use one part Cattlyst 50G Type A Medicated Article with nine parts of feed ingredients to prepare an intermediate blend before preparing a Type C Medicated Feed.

TABLE 2 - Type C Medicated Feed
Pounds of Cattlyst 50G per ton of complete Type C medicated feed | Pounds of a 1,000 g/ton Type B medicated feed per ton of complete Type C medicated feed | Laidlomycin propionate potassium concentration in complete Type C medicated feed (g/ton)
0.1 | 10 | 5
0.15 | 15 | 7.5
0.20 | 20 | 10

Feeding Directions

Feed the Type C medicated feed as the sole ration.

Animal Safety Warning

Do not allow horses or other equines access to feeds containing laidlomycin propionate potassium (Cattlyst 50G). The safety of laidlomycin propionate potassium (Cattlyst 50G) in unapproved species has not been established.

User Safety Warnings

When mixing and handling Cattlyst 50G use appropriate protective clothing, eye, face, and respiratory protection. If accidental eye or skin contact occurs, rinse immediately with water. Operators should wash thoroughly with soap and water after handling Cattlyst 50G.

Keep container closed between uses.

Store below 25°C (77°F), excursions permitted to 37°C (99°F).

Restricted Drug (California) - Use Only as Directed. Not for human use.

WITHDRAWAL PERIODS

No withdrawal period is required when used according to labeling.

Distributed by:
Phibro Animal Health Corporation
Teaneck, NJ 07666

Net Wt 50 LB (22.68 kg)

176-9014-03

Cattlyst 50 Label

Label